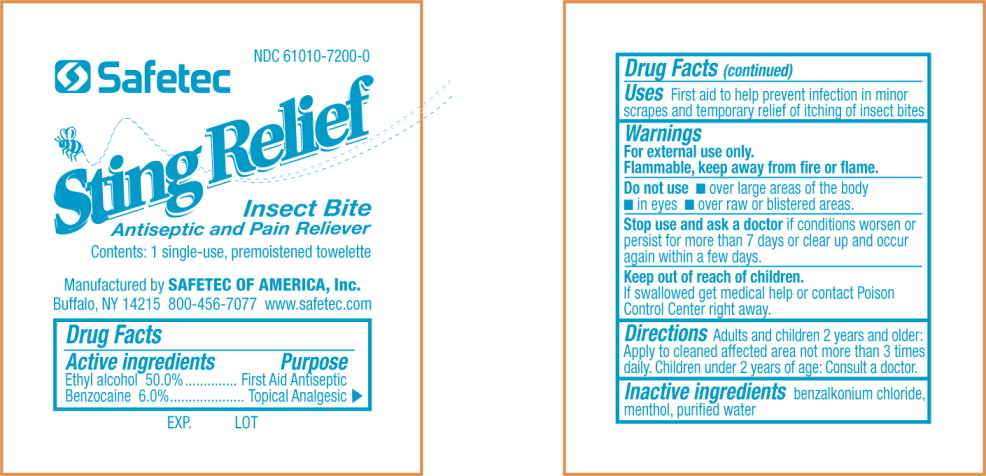 DRUG LABEL: Antiseptic
NDC: 61010-7200 | Form: LIQUID
Manufacturer: Safetec of America, Inc.
Category: otc | Type: HUMAN OTC DRUG LABEL
Date: 20110512

ACTIVE INGREDIENTS: alcohol 500 mg/1 g; benzocaine 60 mg/1 g
INACTIVE INGREDIENTS: benzalkonium chloride; menthol; water

Drug Facts

Active Ingredients

Ethyl alcohol 50.0%

Benzocaine 6.0%

Purpose

First Aid Antiseptic

Topical Analgesic

Uses

First aid to help prevent infection in minor scrapes and temporary relief of itching of insect bites

Warnings

For external use only.

Flammable, keep away from fire or flame.

Do not use

- over large areas of the body
- in eyes
- over raw or blistered areas

Stop use and ask doctor if conditions worsen or persist for more than 7 days or clear up and occur again within a few days.

Keep out of reach of children

If swallowed get medical help or contact a Poison Control Center right away

Directions

Adults and children 2 years and older: Apply to cleaned affected area not more than 3 times daily. Children under 2 years of age: Consult a doctor.

Inactive ingredients

benzalkonium chloride, menthol, purified water

PRINCIPAL DISPLAY PANEL – pouch label

NDC 61010-7200-0

Safetec

Sting Relief
Insect Bite
Antiseptic and Pain Reliever

Contents: 1 single-use, premoistened towelette

Manufactured by SAFETEC OF AMERICA, Inc.
Buffalo, NY 14215 800-456-7077 www.safetec.com

EXP. LOT